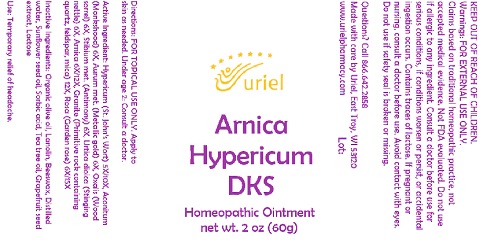 DRUG LABEL: Arnica Hypericum DKS
NDC: 48951-1350 | Form: OINTMENT
Manufacturer: Uriel Pharmacy, Inc.
Category: homeopathic | Type: HUMAN OTC DRUG LABEL
Date: 20210804

ACTIVE INGREDIENTS: URTICA DIOICA 6 [hp_X]/1 g; SEDUM ROSEUM WHOLE 6 [hp_X]/1 g; ARNICA MONTANA FLOWER 6 [hp_X]/1 g; GOLD 6 [hp_X]/1 g; PENOXSULAM 12 [hp_X]/1 g; ACONITUM NAPELLUS 6 [hp_X]/1 g; OXALIS STRICTA WHOLE 6 [hp_X]/1 g; ANTIMONY 6 [hp_X]/1 g; ST. JOHN'S WORT 5 [hp_X]/1 g
INACTIVE INGREDIENTS: CITRUS PARADISI SEED; LACTOSE, UNSPECIFIED FORM; OLIVE OIL; LANOLIN; YELLOW WAX; WATER; TEA TREE OIL; SUNFLOWER OIL; SORBIC ACID

Arnica Hypericum DKS

INDICATIONS AND USAGE

Directions: FOR TOPICAL USE ONLY

DOSAGE AND ADMINISTRATION

Apply to skin as needed. Under age 2: Consult a doctor.

Active Ingredient: Hypericum (St. John’s Wort) 5X/10X, Aconitum (Monkshood) 6X, Aurum met. (Metallic gold) 6X, Oxalis (Wood sorrel) 6X, Stibium met. (Antimony) 6X, Urtica dioica (Stinging nettle) 6X, Arnica 6X/12X, Granite (Primitive rock containing quartz, feldspar, mica) 12X, Rosa (Garden rose) 6X/15X

INACTIVE INGREDIENT

Inactive Ingredients: Organic olive oil, Lanolin, Beeswax, Distilled water, Sunflower seed oil, Sorbic acid, Tea tree oil, Grapefruit seed extract, Lactose

PURPOSE

Use: Temporary relief of headache.

KEEP OUT OF REACH OF CHILDREN.

Warnings: FOR EXTERNAL USE ONLY.
Claims based on traditional homeopathic practice, not accepted medical evidence.
Not FDA evaluated. Do not use if allergic to any ingredient. Consult a doctor before use for serious conditions, if conditions worsen or persist, or accidental ingestion occurs. Contains traces of lactose. If pregnant or nursing, consult a doctor before use. Avoid contact with eyes. Do not use if safety seal is broken or missing.

Questions? Call 866.642.2858
Made with care by Uriel, East Troy, WI 53120
www.urielpharmacy.com Lot#